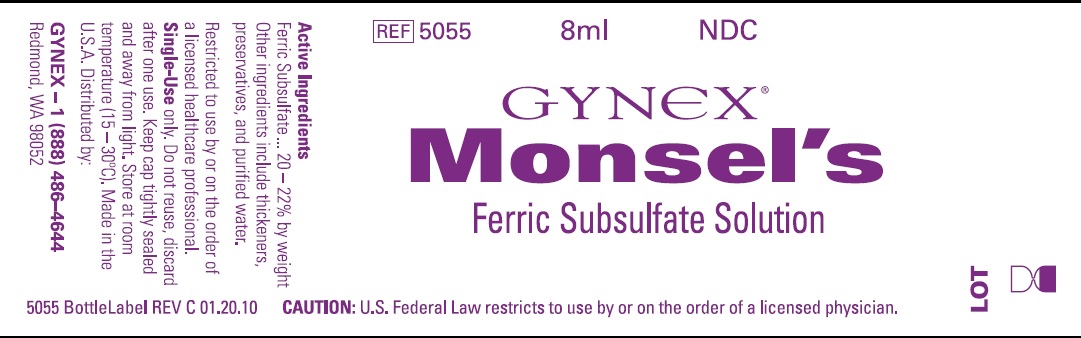 DRUG LABEL: Monsels Solution
NDC: 48992-001 | Form: PASTE
Manufacturer: Gynex Corporation
Category: prescription | Type: HUMAN PRESCRIPTION DRUG LABEL
Date: 20211025

ACTIVE INGREDIENTS: FERRIC SUBSULFATE 210 mg/1 g
INACTIVE INGREDIENTS: SILICON DIOXIDE; FERRIC SULFATE; SODIUM BENZOATE; WATER

Active Ingredients:

Ferric Subsulfate...20-22% by weight

INACTIVE INGREDIENT

Other ingredients include thickeners, preservatives and purified water.

DOSAGE AND ADMINISTRATION

Restricted to use by or on the order of a licensed healthcare professional.

Single-Use only. Do not reuse, discard after one use.

STORAGE AND HANDLING

Keep cap tightly sealed and away from light.

Store at room temperature (15-30°C).